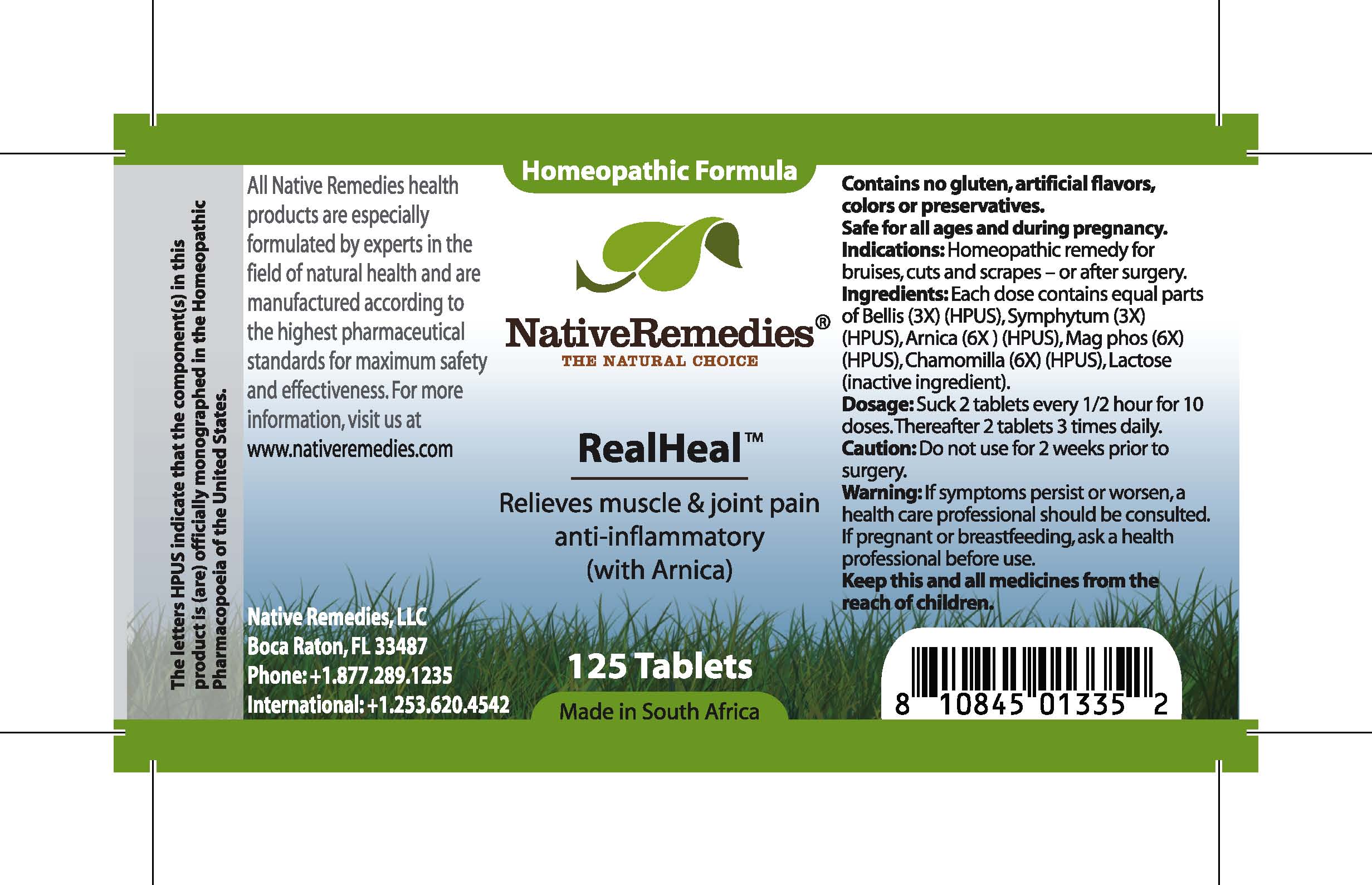 DRUG LABEL: RealHeal
NDC: 68647-140 | Form: TABLET
Manufacturer: Feelgood Health
Category: homeopathic | Type: HUMAN OTC DRUG LABEL
Date: 20100720

ACTIVE INGREDIENTS: BELLIS PERENNIS 3 [hp_X]/1 1; COMFREY ROOT 3 [hp_X]/1 1; ARNICA MONTANA 6 [hp_X]/1 1; MAGNESIUM PHOSPHATE, DIBASIC TRIHYDRATE 6 [hp_X]/1 1; CHAMOMILE 6 [hp_X]/1 1
INACTIVE INGREDIENTS: LACTOSE

REALHEAL

DESCRIPTION

Relieves muscle and joint pain anti-inflammatory (with Arnica)

INDICATIONS AND USAGE

Indications: Homeopathic remedy for bruises, cuts and scrapes – or after surgery.

DOSAGE AND ADMINISTRATION

Dosage: Dissolve 2 tablets every 1/2 hour for 10 doses. Thereafter 2 tablets 3 times daily.

GENERAL PRECAUTIONS

Caution: Do not use for 2 weeks prior to surgery. If symptoms persist or worsen, a health care professional should be consulted. Keep this and all medicines from the reach of children.

ACTIVE INGREDIENT

Ingredients: Each dose contains equal parts of Bellis (3X) (HPUS), Symphytum (3X) (HPUS), Arnica (6X) (HPUS), Mag phos (6X) (HPUS), Chamomilla (6X) (HPUS)

Lactose (inactive ingredient).

PREGNANCY

If pregnant or breastfeeding, ask a health professional before use.

USER SAFETY WARNINGS

Contains no gluten, artificial flavors, colors or preservatives. Safe for all ages and during pregnancy.

PATIENT COUNSELING INFORMATION

All Native Remedies health products are especially formulated by experts in the field of natural health and are manufactured according to the highest pharmaceutical standards for maximum safety and effectiveness. For more information, visit us at www.nativeremedies.com

Distributed by

Native Remedies, LLC

6531 Park of Commerce Blvd.

Suite 160

Boca Raton, FL 33487

Phone: 1.877.289.1235

International: + 1.561.999.8857

The letters HPUS indicate that the component(s) in this product is (are) officially monographed in the Homeopathic Pharmacopoeia of the United States.